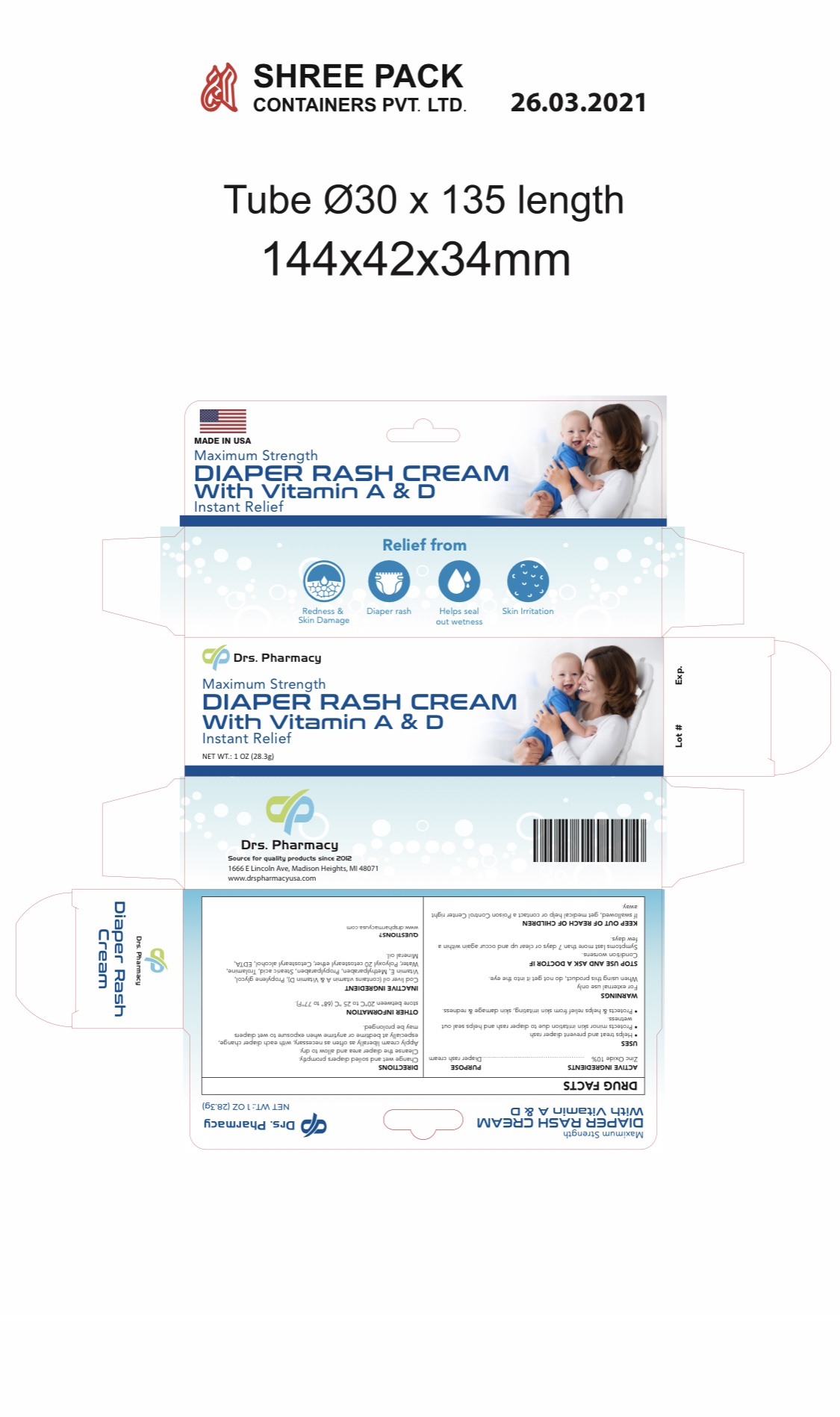 DRUG LABEL: OLP  diaper Rash cream A and D
NDC: 80489-444 | Form: CREAM
Manufacturer: OL PHARMA TECH, LLC Drs PHARMACY
Category: otc | Type: HUMAN OTC DRUG LABEL
Date: 20250109

ACTIVE INGREDIENTS: ZINC OXIDE 10 g/100 g
INACTIVE INGREDIENTS: .ALPHA.-TOCOPHEROL; PROPYLENE GLYCOL; COD LIVER OIL; STEARIC ACID; PROPYLPARABEN; WATER; POLYOXYL 20 CETOSTEARYL ETHER; CETOSTEARYL ALCOHOL; TROLAMINE; MINERAL OIL; EDETATE DISODIUM

Active Ingredients

Zinc Oxide 10%

Stop using this product and ask a doctor

- condition worsens
- symptoms last more than 7 days or clear up and occur again within a few days

Uses

- helps treat and prevent diaper rash
- protects minor skin irritation due to diaper rash and helps seal out wetness

Warning

- For external use only
- when using this product, do not get it into the eye

questions

www.drspharmacyusa.com

Keep out of reach of children. If swallowed, get medical help or contact a Poison Control Center right away.

Directions

- change wet and soiled diapers promptly
- cleanse the diaper area, and allow to dry
- apply cream liberally as often as necessary, with each diaper change, especially at bedtime or anytime when exposure to wet diapers may be prolonged

STORAGE AND HANDLING

store between 20°C to 25 °C (68° to 77°F)

Inactive Ingredients

cod liver oil (contains vitamin A & Vitamin D), propylene glycol, vitamin E, methylparaben, propylparaben, stearic acid, trolamine, ceteareth 20, cetostearyl alcohol, EDTA, mineral oil

purpose

diaper rash cream